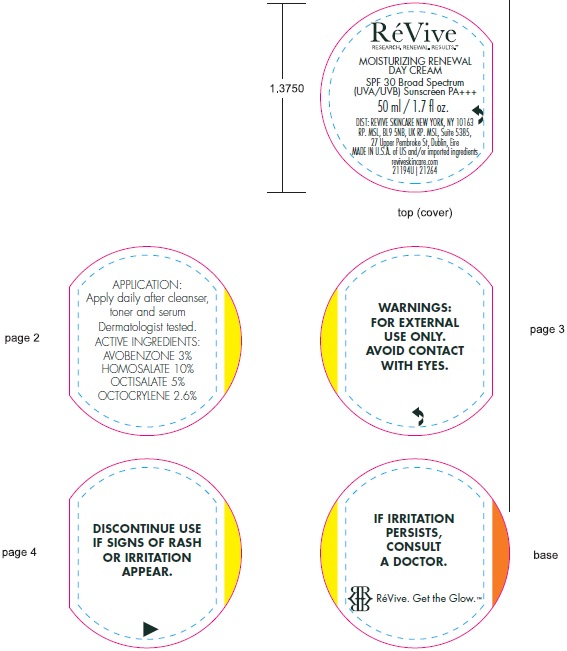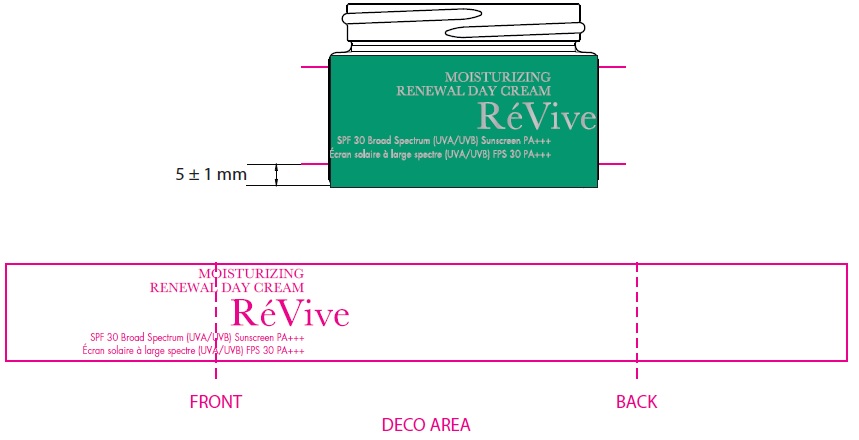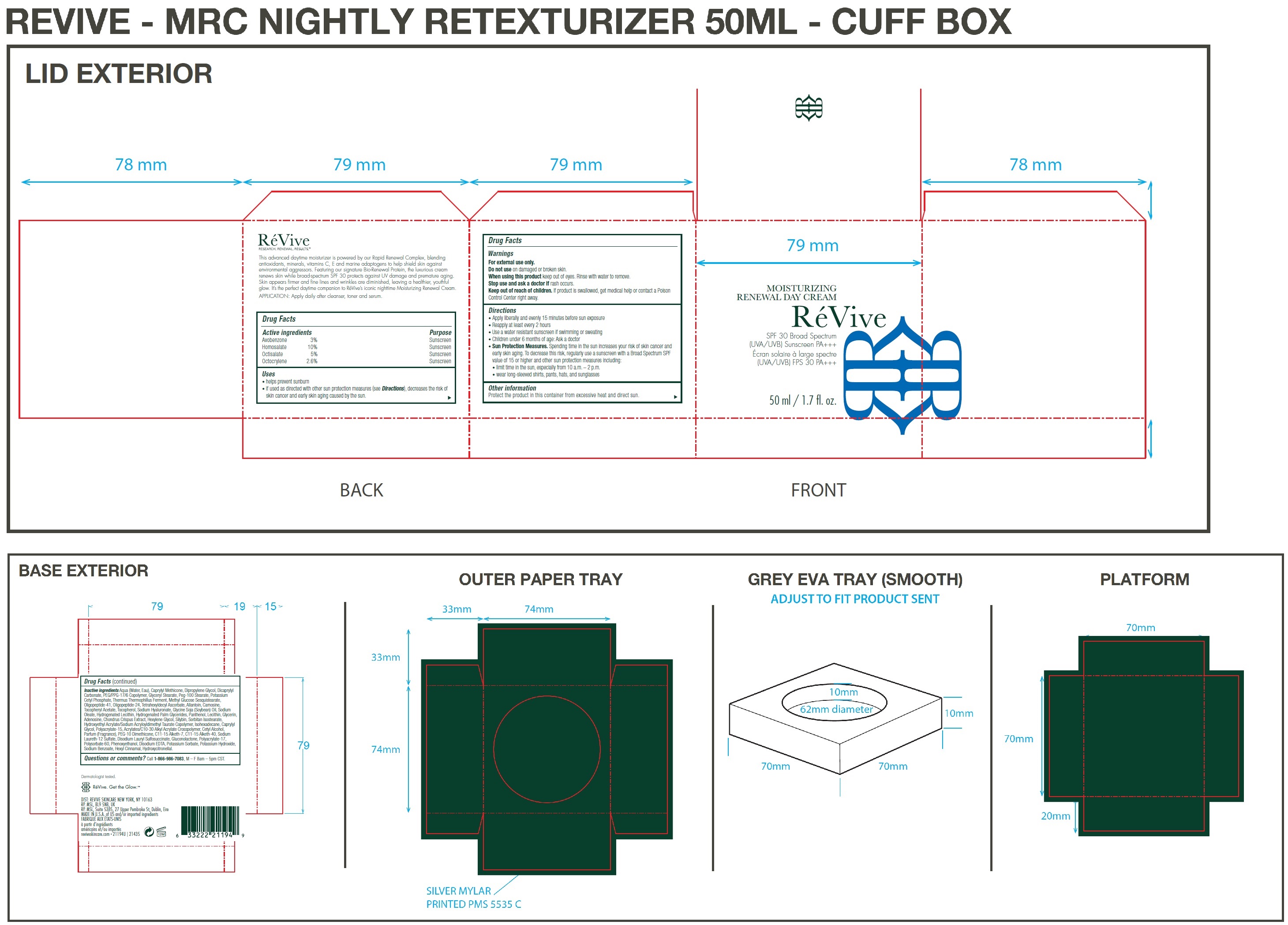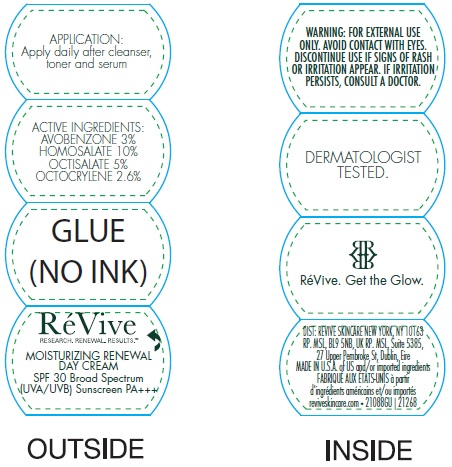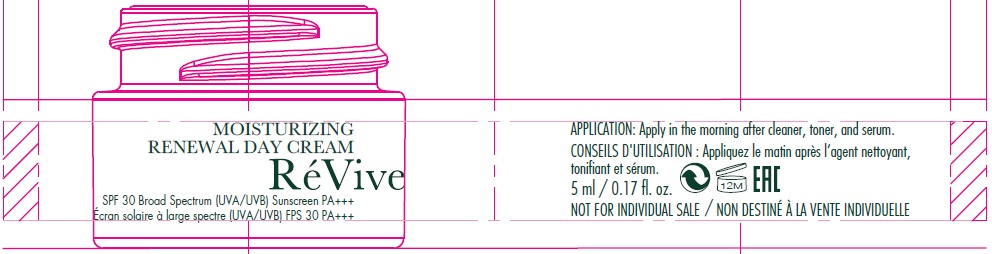 DRUG LABEL: Moisturizing Renewal Cream Broad Spectrum SPF 30 US
NDC: 82691-143 | Form: CREAM
Manufacturer: RV Skincare LLC
Category: otc | Type: HUMAN OTC DRUG LABEL
Date: 20231106

ACTIVE INGREDIENTS: AVOBENZONE 30 mg/1 mL; HOMOSALATE 100 mg/1 mL; OCTISALATE 50 mg/1 mL; OCTOCRYLENE 26 mg/1 mL
INACTIVE INGREDIENTS: WATER; CAPRYLYL TRISILOXANE; DIPROPYLENE GLYCOL; DICAPRYLYL CARBONATE; PEG/PPG-17/6 COPOLYMER; GLYCERYL MONOSTEARATE; PEG-100 STEARATE; POTASSIUM CETYL PHOSPHATE; THERMUS THERMOPHILUS LYSATE; METHYL GLUCOSE SESQUISTEARATE; TETRAHEXYLDECYL ASCORBATE; ALLANTOIN; CARNOSINE; .ALPHA.-TOCOPHEROL ACETATE; TOCOPHEROL; HYALURONATE SODIUM; SOYBEAN OIL; SODIUM OLEATE; HYDROGENATED PALM GLYCERIDES; PANTHENOL; GLYCERIN; ADENOSINE; CHONDRUS CRISPUS CARRAGEENAN; HEXYLENE GLYCOL; SILIBININ; SORBITAN ISOSTEARATE; CAPRYLYL GLYCOL; CETYL ALCOHOL; SODIUM LAURETH-12 SULFATE; DISODIUM LAURYL SULFOSUCCINATE; GLUCONOLACTONE; POLYSORBATE 60; PHENOXYETHANOL; EDETATE DISODIUM ANHYDROUS; POTASSIUM SORBATE; POTASSIUM HYDROXIDE; SODIUM BENZOATE; .ALPHA.-HEXYLCINNAMALDEHYDE; HYDROXYCITRONELLAL

Moisturizing Renewal Cream Broad Spectrum SPF 30 US

Active ingredients

Avobenzone 3%

Homosalate 10%

Octisalate 5%

Octocrylene 2.6%

Purpose

Sunscreen

Uses

• helps prevent sunburn

• if used as directed with other sun protection measures (see Directions), decreases the risk of skin cancer and early skin aging caused by the sun.

Warnings

For external use only.

Do not use

on damaged or broken skin.

When using this product

keep out of eyes. Rinse with water to remove.

Stop use and ask a doctor if

rash occurs.

Keep out of reach of children.

If product is swallowed, get medical help or contact a Poison Control Center right away.

Directions

• Apply liberally and evenly 15 minutes before sun exposure • Reapply at least every 2 hours • Use a water resistant sunscreen if swimming or sweating • Children under 6 months of age: Ask a doctor • Spending time in the sun increases your risk of skin cancer and early skin aging. To decrease this risk, regularly use a sunscreen with a Broad Spectrum SPF value of 15 or higher and other sun protection measures including: • limit time in the sun, especially from 10 a.m. – 2 p.m. • wear long-sleeved shirts, pants, hats, and sunglasses
Sun Protection Measures.

Other information

Protect the product in this container from excessive heat and direct sun.

Inactive ingredients:

Aqua (Water, Eau), Caprylyl Methicone, Dipropylene Glycol, Dicaprylyl Carbonate, PEG/PPG-17/6 Copolymer, Glyceryl Stearate, Peg-100 Stearate, Potassium Cetyl Phosphate, Thermus Thermophillus Ferment, Methyl Glucose Sesquistearate, Oligopeptide-41, Oligopeptide-24, Tetrahexyldecyl Ascorbate, Allantoin, Carnosine, Tocopheryl Acetate, Tocopherol, Sodium Hyaluronate, Glycine Soja (Soybean) Oil, Sodium Oleate, Hydrogenated Lecithin, Hydrogenated Palm Glycerides, Panthenol, Lecithin, Glycerin, Adenosine, Chondrus Crispus Extract, Hexylene Glycol, Silybin, Sorbitan Isostearate, Hydroxyethyl Acrylate/Sodium Acryloyldimethyl Taurate Copolymer, Isohexadecane, Caprylyl Glycol, Polyacrylate-15, Acrylates/C10-30 Alkyl Acrylate Crosspolymer, Cetyl Alcohol, Parfum (Fragrance), PEG-10 Dimethicone, C11-15 Alketh-7, C11-15 Alketh-40, Sodium Laureth-12 Sulfate, Disodium Lauryl Sulfosuccinate, Gluconolactone, Polyacrylate-17, Polysorbate 60, Phenoxyethanol, Disodium EDTA, Potassium Sorbate, Potassium Hydroxide, Sodium Benzoate, Hexyl Cinnamal, Hydroxycitronellal.

Questions or comments?

Call , M – F 8am – 5pm CST. 1-866-986-7083